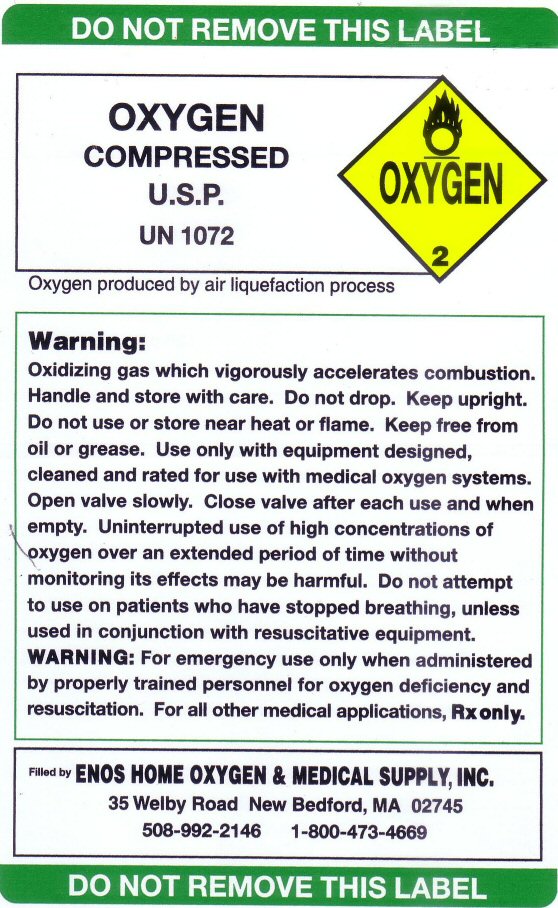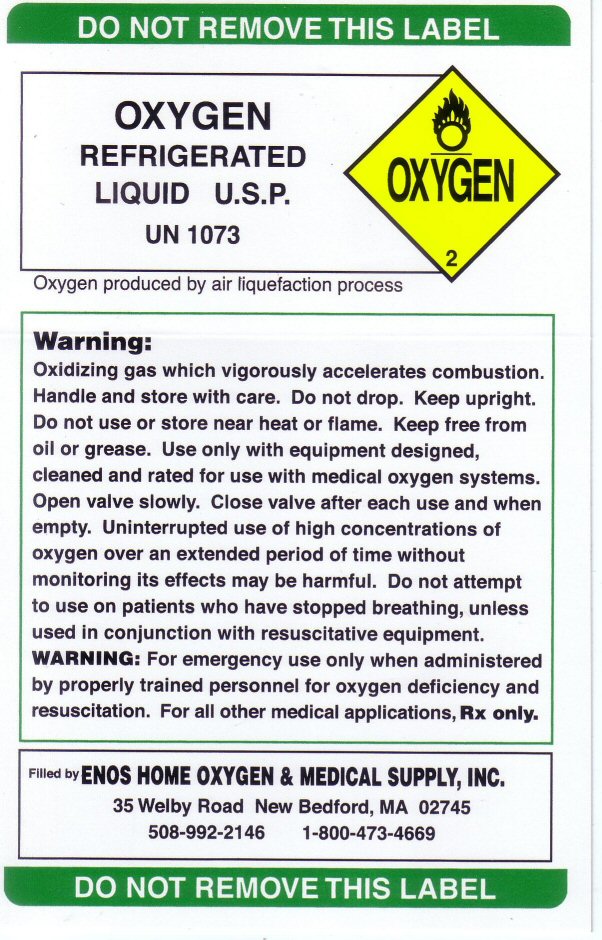 DRUG LABEL: OXYGEN
NDC: 58987-001 | Form: GAS
Manufacturer: Enos Home Oxygen Therapy, Inc.
Category: prescription | Type: HUMAN PRESCRIPTION DRUG LABEL
Date: 20251125

ACTIVE INGREDIENTS: OXYGEN 99.5 L/100 L

WARNINGS AND PRECAUTIONS

WARNING: For emergency use only when administered by properly trained personnel for oxygen deficiency and resuscitation. For all other medical applications Rx only.

DO NOT REMOVE THIS LABEL

OXYGEN COMPRESSED LABEL

OXYGEN COMPRESSED U.S.P. UN 1072 Oxygen produced by air liquefaction Warning: Oxidizing gas which vigorously accelerates combustion. Handle and store with care. Do not drop. Keep upright. Do not use or store near heat or flame. Keep free from oil or grease. Use only with equipment designed, cleaned and rated for use with medical oxygen systems. Open valve slowly. Close valve after each use and when empty. Uninterrupted use of high concentrations of oxygen over an extended period of time without monitoring its effects may be harmful. Do not attempt to use on patients who have stopped breathing, unless used in conjunction with resuscitative equipment.
Filled by: ENOS HOME OXYGEN AND MEDICAL SUPPLY, INC.
35 Welby Road New Bedford, MA 02745
508-992-2146 1-800-473-4669

OXYGEN REFRIGERATED LIQUID LABEL

OXYGEN REFRIGERATED LIQUID U.S.P. UN 1073Oxygen produced by air liquefaction Warning: Oxidizing gas which vigorously accelerates combustion. Handle and store with care. Do not drop. Keep upright. Do not use or store near heat or flame. Keep free from oil or grease. Use only with equipment designed, cleaned and rated for use with medical oxygen systems. Open valve slowly. Close valve after each use and when empty. Uninterrupted use of high concentrations of oxygen over an extended period of time without monitoring its effects may be harmful. Do not attempt to use on patients who have stopped breathing, unless used in conjunction with resuscitative equipment.

Filled by: ENOS HOME OXYGEN AND MEDICAL SUPPLY, INC.
35 Welby Road New Bedford, MA 02745
508-992-2146 1-800-473-4669